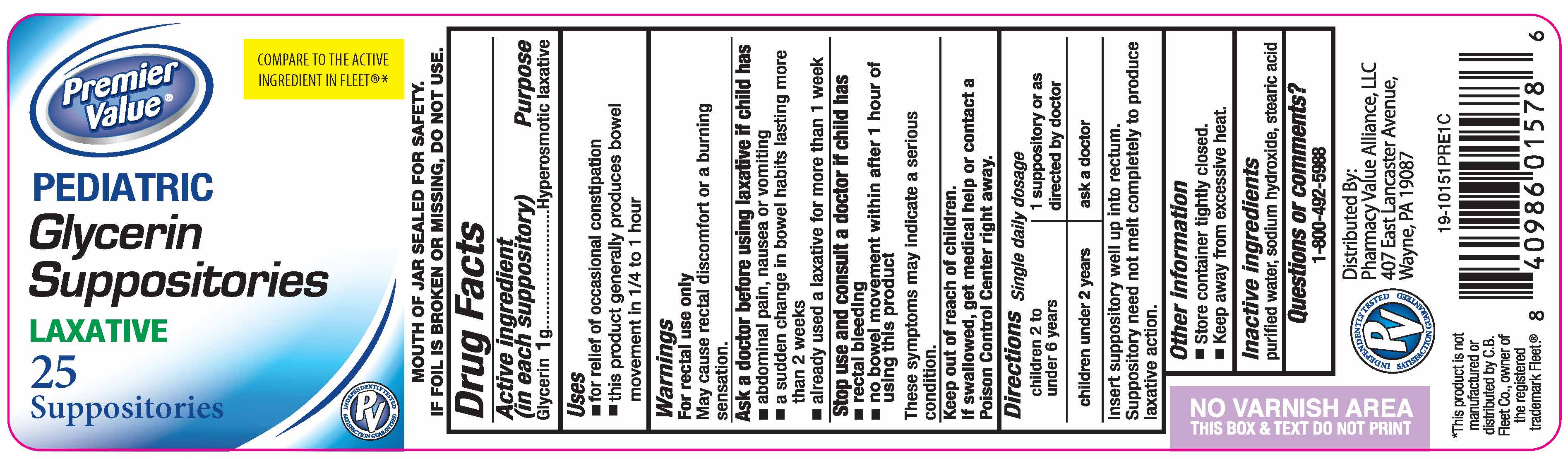 DRUG LABEL: Glycerin								
NDC: 68016-161 | Form: SUPPOSITORY
Manufacturer: Chain Drug Consortium LLC
Category: otc | Type: HUMAN OTC DRUG LABEL
Date: 20251024

ACTIVE INGREDIENTS: GLYCERIN 1 g/1 1
INACTIVE INGREDIENTS: WATER; SODIUM HYDROXIDE; STEARIC ACID

Premier Value Pediatric Glycerin Supp

Active ingredient (in each suppository)

Glycerin 1 g

Purpose

Hyperosmotic laxative

Uses

- for relief of occasional constipation
- this product generally produces a bowel movement in 1/4 to 1 hour

Warnings

For rectal use only

May cause rectal discomfort of burning sensation

Ask a Doctor before using laxative if child has

- abdominal pain, nausea or vomiting
- a sudden change in bowel habits lasting more than two weeks
- already used a laxative for more than 1 week

Stop use and consult a doctor if child has

- rectal bleeding
- no bowel movement within 1 hour of using this product

These symptoms may indicate a serious condition.

Keep out of reach of children.

If swallowed, get medical help or contact a Poison Control Center right away.

Directions

Single daily dosage
children 2 to under 6 years | 1 suppository or as directed by a doctor
children under 2 years | ask a doctor

Insert suppository well up intorectum.

Suppository need not melt completely to produce laxative action.

Other information

- Store container tightly closed.
- Keep away from excessive heat.

Inactive ingredients

purified water, sodium hydroxide, stearic acid

Pediatric Glycerin Suppositories, 25 count

PremVal722.jpg

The product package shown above represents a sample of that currently in use. Additional packaging may also be available.

PediatricGlycerin Suppositories, 25 count

Distributed by Pharmacy Value Alliance, LLC

407 East Lancaster Avenue

Wayne, PA 19087